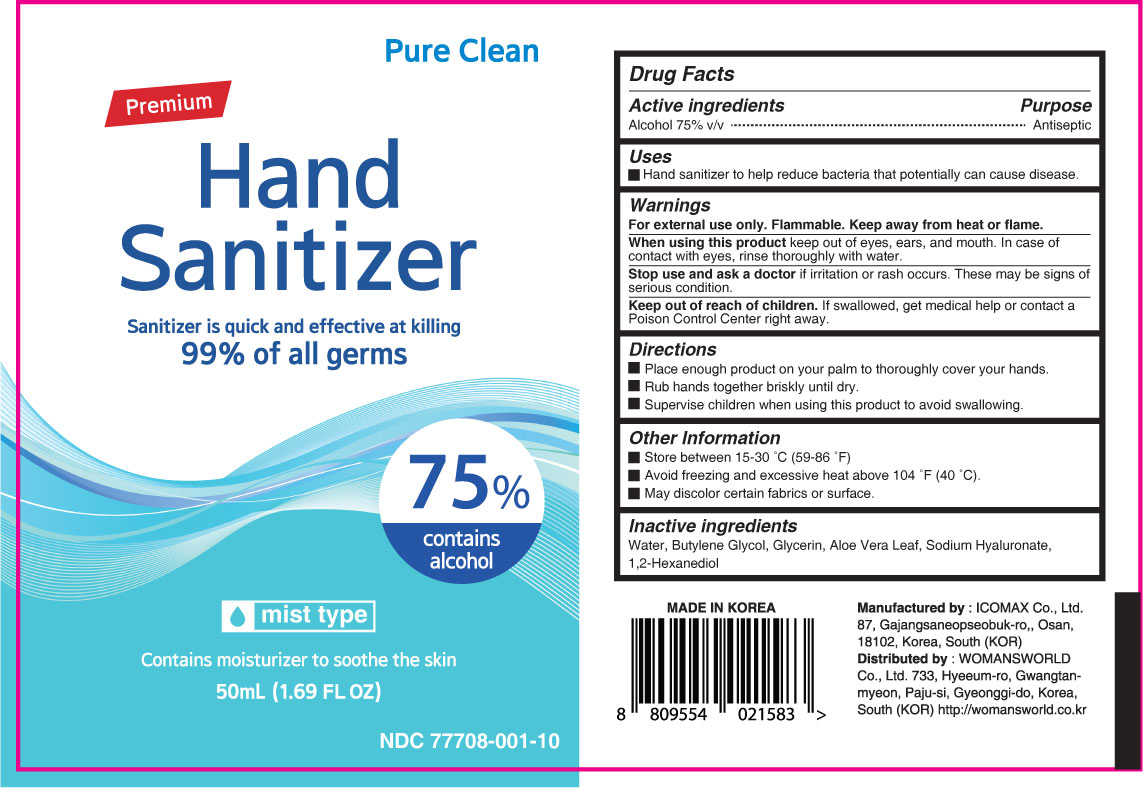 DRUG LABEL: Pure Clean Premium Hand Sanitizer
NDC: 77708-001 | Form: LIQUID
Manufacturer: WOMANSWORLD Co., Ltd.
Category: otc | Type: HUMAN OTC DRUG LABEL
Date: 20200608

ACTIVE INGREDIENTS: ALCOHOL 75 mL/100 mL
INACTIVE INGREDIENTS: BUTYLENE GLYCOL; HYALURONATE SODIUM; 1,2-HEXANEDIOL; ALOE VERA LEAF; WATER; GLYCERIN

Active Ingredient

Alcohol 75% v/v

Purpose

Antiseptic

Use

- Hand sanitizer to help reduce bacteria that potentially can cause disease.

Warnings

For external use only. Flammable. Keep away from heat or flame.

When using this product keep out of eyes, ears, and mouth. In case of contact with eyes, rinse thoroughly with water.

Stop use and ask a doctor if irritation or rash occurs. These may be signs of serious condition.

Keep out of reach of children. If swallowed, get medical help or contact a Poison Control Center right away.

Directions

- Place enough product on your palm to thoroughly cover your hands.
- Rub hands together briskly until dry.
- Supervise children when using this product to avoid swallowing.

Other Information

- Store between 15-30 °C (59-86°F).
- Avoid freezing and excessive heat above 104°F(40°C).
- May discolor certain fabrics or surface.

Inactive Ingredients

Water, Butylene Glycol, Glycerin, Aloe Vera Leaf, Sodium Hyaluronate, 1,2-Hexanediol